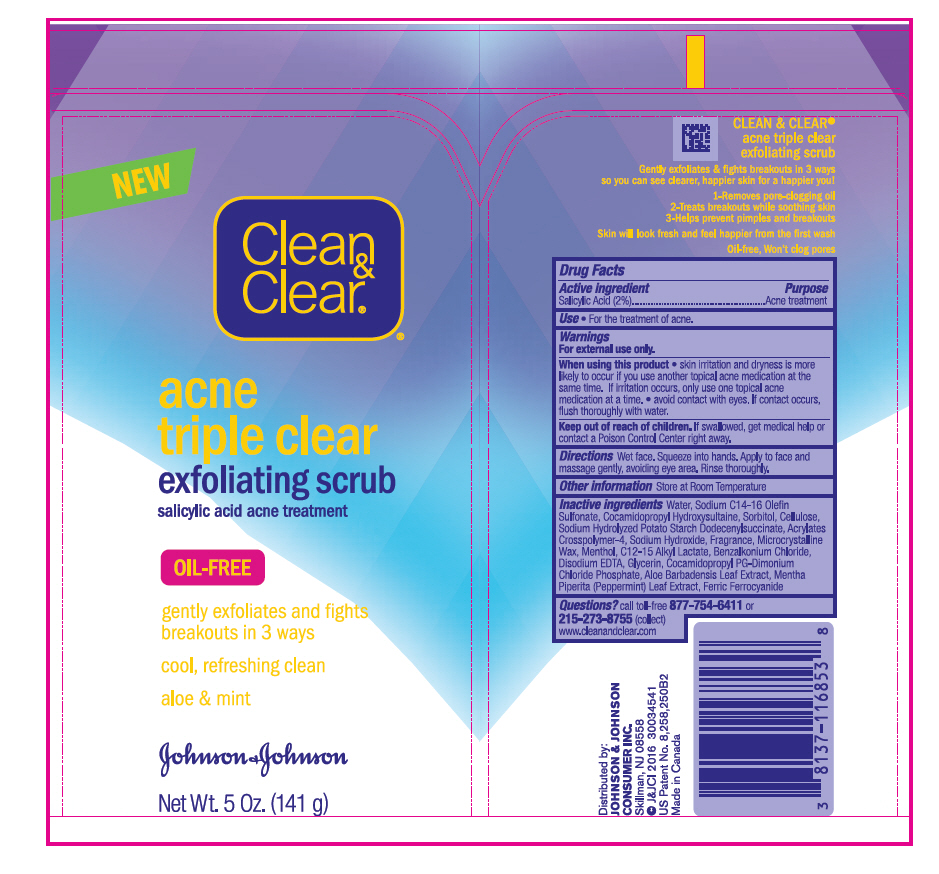 DRUG LABEL: Clean and Clear acne triple clear exfoliating scrub
NDC: 69968-0013 | Form: GEL
Manufacturer: Kenvue Brands LLC
Category: otc | Type: HUMAN OTC DRUG LABEL
Date: 20241106

ACTIVE INGREDIENTS: SALICYLIC ACID 20 mg/1 g
INACTIVE INGREDIENTS: WATER; COCAMIDOPROPYL HYDROXYSULTAINE; SODIUM C14-16 OLEFIN SULFONATE; GLYCERIN; SODIUM HYDROXIDE; FERRIC FERROCYANIDE; ALOE VERA LEAF; MENTHOL, UNSPECIFIED FORM; EDETATE DISODIUM ANHYDROUS; COCAMIDOPROPYL PROPYLENE GLYCOL-DIMONIUM CHLORIDE PHOSPHATE; POWDERED CELLULOSE; MENTHA PIPERITA LEAF; BENZALKONIUM CHLORIDE; MICROCRYSTALLINE WAX; C12-15 ALKYL LACTATE; SORBITOL

Clean & Clear® acne triple clear exfoliating scrub

Drug Facts

Active ingredient

Salicylic Acid (2%)

Purpose

Acne treatment

Use

- For the treatment of acne.

Warnings

For external use only.

When using this product

- skin irritation and dryness is more likely to occur if you use another topical acne medication at the same time. If irritation occurs, only use one topical acne medication at a time.
- avoid contact with eyes. If contact occurs, flush thoroughly with water.

Keep out of reach of children. If swallowed, get medical help or contact a Poison Control Center right away.

Directions

Wet face. Squeeze into hands. Apply to face and massage gently, avoiding eye area. Rinse thoroughly.

Other information

Store at Room Temperature

Inactive ingredients

Water, Sodium C14-16 Olefin Sulfonate, Cocamidopropyl Hydroxysultaine, Sorbitol, Cellulose, Sodium Hydrolyzed Potato Starch Dodecenylsuccinate, Acrylates Crosspolymer-4, Sodium Hydroxide, Fragrance, Microcrystalline Wax, Menthol, C12-15 Alkyl Lactate, Benzalkonium Chloride, Disodium EDTA, Glycerin, Cocamidopropyl PG-Dimonium Chloride Phosphate, Aloe Barbadensis Leaf Extract, Mentha Piperita (Peppermint) Leaf Extract, Ferric Ferrocyanide

Questions?

call toll-free 877-754-6411 or 215-273-8755 (collect) www.cleanandclear.com

Distributed by:
JOHNSON & JOHNSON
CONSUMER INC.
Skillman, NJ 08558

PRINCIPAL DISPLAY PANEL - 141 g Tube Label

NEW
Clean
&
Clear®®

acne
triple clear
exfoliating scrub
salicylic acid acne treatment

OIL-FREE

gently exfoliates and fights
breakouts in 3 ways

cool, refreshing clean
aloe + mint

Johnson & Johnson

Net Wt. 5 Oz. (141 g)